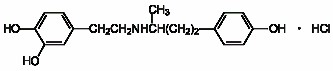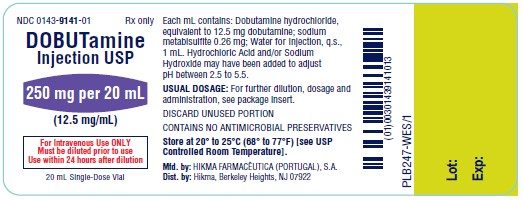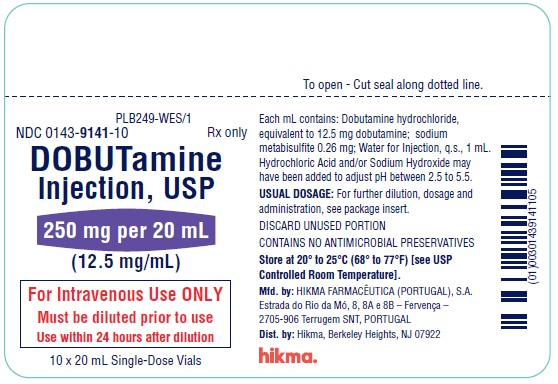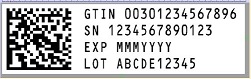 DRUG LABEL: Dobutamine
NDC: 0143-9141 | Form: INJECTION, SOLUTION
Manufacturer: Hikma Pharmaceuticals USA Inc.
Category: prescription | Type: HUMAN PRESCRIPTION DRUG LABEL
Date: 20240702

ACTIVE INGREDIENTS: DOBUTAMINE HYDROCHLORIDE 12.5 mg/1 mL
INACTIVE INGREDIENTS: SODIUM METABISULFITE .26 mg/1 mL; HYDROCHLORIC ACID; SODIUM HYDROXIDE; WATER

DOBUTamine Injection USP
Rx ONLY

DESCRIPTION

Dobutamine Injection USP is (±)-4-[2-[[3-(p-Hydroxyphenyl)-1-methylpropyl]amino]ethyl]-pyrocatechol hydrochloride. It is a synthetic catecholamine.

Molecular Formula: C18H23NO3•HCl

Molecular Weight: 337.84

The clinical formulation is supplied in a sterile form for intravenous use only. Each mL contains: dobutamine hydrochloride, equivalent to 12.5 mg (41.5 µmol) dobutamine; sodium metabisulfite 0.26 mg, and water for injection, q.s. Hydrochloric acid and/or sodium hydroxide may have been added during manufacture to adjust the pH (2.5 to 5.5).

CLINICAL PHARMACOLOGY

Dobutamine is a direct-acting inotropic agent whose primary activity results from stimulation of the ß receptors of the heart while producing comparatively mild chronotropic, hypertensive, arrhythmogenic, and vasodilative effects. It does not cause the release of endogenous norepinephrine, as does dopamine. In animal studies, dobutamine produces less increase in heart rate and less decrease in peripheral vascular resistance for a given inotropic effect than does isoproterenol.

In patients with depressed cardiac function, both dobutamine and isoproterenol increase the cardiac output to a similar degree. In the case of dobutamine, this increase is usually not accompanied by marked increases in heart rate (although tachycardia is occasionally observed), and the cardiac stroke volume is usually increased. In contrast, isoproterenol increases the cardiac index primarily by increasing the heart rate while stroke volume changes little or declines.

Facilitation of atrioventricular conduction has been observed in human electrophysiologic studies and in patients with atrial fibrillation.

Systemic vascular resistance is usually decreased with administration of dobutamine. Occasionally, minimum vasoconstriction has been observed.

Most clinical experience with dobutamine is short-term–not more than several hours in duration. In the limited number of patients who were studied for 24, 48, and 72 hours, a persistent increase in cardiac output occurred in some, whereas output returned toward baseline values in others.

The onset of action of dobutamine is within 1 to 2 minutes; however, as much as 10 minutes may be required to obtain the peak effect of a particular infusion rate.

The plasma half-life of dobutamine in humans is 2 minutes. The principal routes of metabolism are methylation of the catechol and conjugation. In human urine, the major excretion products are the conjugates of dobutamine and 3-O-methyl dobutamine. The 3-O-methyl derivative of dobutamine is inactive.

Alteration of synaptic concentrations of catecholamines with either reserpine or tricyclic antidepressants does not alter the actions of dobutamine in animals, which indicates that the actions of dobutamine are not dependent on presynaptic mechanisms.

The effective infusion rate of dobutamine varies widely from patient to patient, and titration is always necessary (see DOSAGE AND ADMINISTRATION). At least in pediatric patients, dobutamine-induced increases in cardiac output and systemic pressure are generally seen, in any given patient, at lower infusion rates than those that cause substantial tachycardia (see PRECAUTIONS, Pediatric Use).

INDICATIONS AND USAGE

Dobutamine is indicated when parenteral therapy is necessary for inotropic support in the short‑term treatment of patients with cardiac decompensation due to depressed contractility resulting either from organic heart disease or from cardiac surgical procedures. Experience with intravenous dobutamine in controlled trials does not extend beyond 48 hours of repeated boluses and/or continuous infusions.

Whether given orally, continuously intravenously, or intermittently intravenously, neither dobutamine nor any other cyclic-AMP-dependent inotrope has been shown in controlled trials to be safe or effective in the long-term treatment of congestive heart failure. In controlled trials of chronic oral therapy with various such agents, symptoms were not consistently alleviated, and the cyclic-AMP-dependent inotropes were consistently associated with increased risk of hospitalization and death. Patients with NYHA Class IV symptoms appeared to be at particular risk.

CONTRAINDICATIONS

Dobutamine is contraindicated in patients with idiopathic hypertrophic subaortic stenosis and in patients who have shown previous manifestations of hypersensitivity to dobutamine.

WARNINGS

Increase in Heart Rate or Blood Pressure

Dobutamine may cause a marked increase in heart rate or blood pressure, especially systolic pressure. Approximately 10% of adult patients in clinical studies have had rate increases of 30 beats/minute or more, and about 7.5% have had a 50 mm Hg or greater increase in systolic pressure. Usually, reduction of dosage promptly reverses these effects. Because dobutamine facilitates atrioventricular conduction, patients with atrial fibrillation are at risk of developing rapid ventricular response. In patients who have atrial fibrillation with rapid ventricular response, a digitalis preparation should be used prior to institution of therapy with dobutamine. Patients with preexisting hypertension appear to face an increased risk of developing an exaggerated pressor response.

Ectopic Activity

Dobutamine may precipitate or exacerbate ventricular ectopic activity, but it rarely has caused ventricular tachycardia.

Hypersensitivity

Reactions suggestive of hypersensitivity associated with administration of dobutamine including skin rash, fever, eosinophilia, and bronchospasm, have been reported occasionally.

Dobutamine contains sodium metabisulfite, a sulfite that may cause allergic-type reactions, including anaphylactic symptoms and life-threatening or less severe asthmatic episodes, in certain susceptible people. The overall prevalence of sulfite sensitivity in the general population is unknown and probably low. Sulfite sensitivity is seen more frequently in asthmatic than in nonasthmatic people.

PRECAUTIONS

General

1. During the administration of dobutamine, as with any adrenergic agent, ECG and blood pressure should be continuously monitored. In addition, pulmonary wedge pressure and cardiac output should be monitored whenever possible to aid in the safe and effective infusion of dobutamine.
2. Hypovolemia should be corrected with suitable volume expanders before treatment with dobutamine is instituted.
3. No improvement may be observed in the presence of marked mechanical obstruction, such as severe valvular aortic stenosis.

Usage Following Acute Myocardial Infarction

Clinical experience with dobutamine following myocardial infarction has been insufficient to establish the safety of the drug for this use. There is concern that any agent that increases contractile force and heart rate may increase the size of an infarction by intensifying ischemia, but it is not known whether dobutamine does so.

Laboratory Tests

Dobutamine, like other ß2-agonists, can produce a mild reduction in serum potassium concentration, rarely to hypokalemic levels. Accordingly, consideration should be given to monitoring serum potassium.

Drug Interactions

Animal studies indicate that dobutamine may be ineffective if the patient has recently received a ß-blocking drug. In such a case, the peripheral vascular resistance may increase.

Preliminary studies indicate that the concomitant use of dobutamine and nitroprusside results in a higher cardiac output and, usually, a lower pulmonary wedge pressure than when either drug is used alone.

There was no evidence of drug interactions in clinical studies in which dobutamine was administered concurrently with other drugs, including digitalis preparations, furosemide, spironolactone, lidocaine, glyceryl trinitrate, isosorbide dinitrate, morphine, atropine, heparin, protamine, potassium chloride, folic acid, and acetaminophen.

Carcinogenesis, Mutagenesis, Impairment of Fertility

Studies to evaluate the carcinogenic or mutagenic potential of dobutamine, or its potential to affect fertility, have not been conducted.

Pregnancy-Teratogenic Effects-Pregnancy Category B

Reproduction studies performed in rats at doses up to the normal human dose (10 mcg/kg/min for 24 h, total daily dose of 14.4 mg/kg), and in rabbits at doses up to twice the normal human dose, have revealed no evidence of harm to the fetus due to dobutamine. There are, however, no adequate and well-controlled studies in pregnant women. Because animal reproduction studies are not always predictive of human response, this drug should be used during pregnancy only if clearly needed.

Labor and Delivery

The effect of dobutamine on labor and delivery is unknown.

Nursing Mothers

It is not known whether this drug is excreted in human milk. Because many drugs are excreted in human milk, caution should be exercised when dobutamine is administered to a nursing woman. If a mother requires dobutamine treatment, breastfeeding should be discontinued for the duration of the treatment.

Pediatric Use

Dobutamine has been shown to increase cardiac output and systemic pressure in pediatric patients of every age group. In premature neonates, however, dobutamine is less effective than dopamine in raising systemic blood pressure without causing undue tachycardia, and dobutamine has not been shown to provide any added benefit when given to such infants already receiving optimal infusions of dopamine.

Geriatric Use

Of the 1893 patients in clinical studies who were treated with dobutamine, 930 (49.1%) were 65 and older. No overall differences in safety or effectiveness were observed between these and younger subjects. Other reported clinical experience has not identified differences in responses between the elderly and younger patients, but greater sensitivity of some older individuals cannot be ruled out.

In general, dose selection for an elderly patient should be cautious, usually starting at the low end of the dosing range, reflecting the greater frequency of decreased hepatic, renal, or cardiac function, and of concomitant disease or drug therapy.

ADVERSE REACTIONS

Increased Heart Rate, Blood Pressure, and Ventricular Ectopic Activity

A 10- to 20-mm increase in systolic blood pressure and an increase in heart rate of 5 to 15 beats/minute have been noted in most patients (see WARNINGS regarding exaggerated chronotropic and pressor effects). Approximately 5% of adult patients have had increased premature ventricular beats during infusions. These effects are dose related.

Hypotension

Precipitous decreases in blood pressure have occasionally been described in association with dobutamine therapy. Decreasing the dose or discontinuing the infusion typically results in rapid return of blood pressure to baseline values. In rare cases, however, intervention may be required and reversibility may not be immediate.

Reactions at Sites of Intravenous Infusion

Phlebitis has occasionally been reported. Local inflammatory changes have been described following inadvertent infiltration. Isolated cases of cutaneous necrosis (destruction of skin tissue) have been reported.

Miscellaneous Uncommon Effects

The following adverse effects have been reported in 1% to 3% of adult patients: nausea, headache, anginal pain, nonspecific chest pain, palpitations, and shortness of breath.

Isolated cases of thrombocytopenia have been reported.

Administration of dobutamine, like other catecholamines, can produce a mild reduction in serum potassium concentration, rarely to hypokalemic levels (see PRECAUTIONS).

OVERDOSAGE

Overdoses of dobutamine have been reported rarely. The following is provided to serve as a guide if such an overdose is encountered.

Signs and Symptoms- Toxicity from dobutamine is usually due to excessive cardiac ß-receptor stimulation. The duration of action of dobutamine is generally short (T1/2= 2 minutes) because it is rapidly metabolized by catechol-0-methyltranferase. The symptoms of toxicity may include anorexia, nausea, vomiting, tremor, anxiety, palpitations, headache, shortness of breath, and anginal and nonspecific chest pain. The positive inotropic and chronotropic effects of dobutamine on the myocardium may cause hypertension, tachyarrhythmias, myocardial ischemia, and ventricular fibrillation. Hypotension may result from vasodilation.

Treatment- To obtain up-to-date information about the treatment of overdose, a good resource is your certified Regional Poison Control Center. Telephone numbers of certified poison control centers are listed in the Physicians’ Desk Reference (PDR). In managing overdosage, consider the possibility of multiple drug overdoses, interaction among drugs, and unusual drug kinetics in your patient.

The initial actions to be taken in a dobutamine overdose are discontinuing administration, establishing an airway, and ensuring oxygenation and ventilation. Resuscitative measures should be initiated promptly. Severe ventricular tachyarrhythmias may be successfully treated with propranolol or lidocaine. Hypertension usually responds to a reduction in dose or discontinuation of therapy.

Protect the patient’s airway and support ventilation and perfusion. If needed, meticulously monitor and maintain, within acceptable limits, the patient’s vital signs, blood gases, serum electrolytes, etc.

If the product is ingested, unpredictable absorption may occur from the mouth and the gastrointestinal tract. Absorption of drugs from the gastrointestinal tract may be decreased by giving activated charcoal, which, in many cases, is more effective than emesis or lavage; consider charcoal instead of or in addition to gastric emptying. Repeated doses of charcoal over time may hasten elimination of some drugs that have been absorbed. Safeguard the patient’s airway when employing gastric emptying or charcoal.

Forced diuresis, peritoneal dialysis, hemodialysis, or charcoal hemoperfusion have not been established as beneficial for an overdose of dobutamine.

DOSAGE AND ADMINISTRATION

Note- Do not add dobutamine to 5% Sodium Bicarbonate Injection or to any other strongly alkaline solution. Because of potential physical incompatibilities, it is recommended that dobutamine not be mixed with other drugs in the same solution. Dobutamine should not be used in conjunction with other agents or diluents containing both sodium bisulfite and ethanol.

Preparation and Stability

At the time of administration, dobutamine must be further diluted in an IV container to at least a 50 mL solution using one of the following intravenous solutions as a diluent: 5% Dextrose Injection, 5% Dextrose and 0.45% Sodium Chloride Injection, 5% Dextrose and 0.9% Sodium Chloride Injection, 10% Dextrose Injection, Isolyte® M with 5% Dextrose Injection, Lactated Ringer’s Injection, 5% Dextrose in Lactated Ringer’s Injection, Normosol®-M in D5-W, 20% Osmitrol® in Water for Injection, 0.9% Sodium Chloride Injection, or Sodium Lactate Injection. Intravenous solutions should be used within 24 hours.

Recommended Dosage

Infusion of dobutamine should be started at a low rate (0.5 to 1 mcg/kg/min) and titrated at intervals of a few minutes, guided by the patient’s response, including systemic blood pressure, urine flow, frequency of ectopic activity, heart rate and (whenever possible) measurements of cardiac output, central venous pressure, and/or pulmonary capillary wedge pressure. In reported trials, the optimal infusion rates have varied from patient to patient, usually 2 to 20 mcg/kg/min but sometimes slightly outside of this range. On rare occasions, infusion rates up to 40 mcg/kg/min have been required to obtain the desired effect. Rates of infusion (mL/h) for dobutamine concentrations of 500 mcg/mL, 1000 mcg/mL, and 2000 mcg/mL necessary to attain various delivery rates of dobutamine (mcg/kg/min) for patients of different weights are given in Table 1.

Table 1 Dobutamine Injection USP Infusion Rate (mL/h) for 500 mcg/mL concentration

Drug Delivery Rate |  |  |  | Patient Body Weight (kg)
(mcg/kg/min) | 5 | 10 | 20 | 30 | 40 | 50 | 60 | 70 | 80 | 90 | 100 | 110
0.5 | 0.3 | 0.6 | 1.2 | 1.8 | 2.4 | 3 | 3.6 | 4.2 | 4.8 | 5.4 | 6 | 6.6
1 | 0.6 | 1.2 | 2.4 | 3.6 | 4.8 | 6 | 7.2 | 8.4 | 9.6 | 10.8 | 12 | 13.2
2.5 | 1.5 | 3 | 6 | 9 | 12 | 15 | 18 | 21 | 24 | 27 | 30 | 33
5 | 3 | 6 | 12 | 18 | 24 | 30 | 36 | 42 | 48 | 54 | 60 | 66
7.5 | 4.5 | 9 | 18 | 27 | 36 | 45 | 54 | 63 | 72 | 81 | 90 | 99
10 | 6 | 12 | 24 | 36 | 48 | 60 | 72 | 84 | 96 | 108 | 120 | 132
12.5 | 7.5 | 15 | 30 | 45 | 60 | 75 | 90 | 105 | 120 | 135 | 150 | 165
15 | 9 | 18 | 36 | 54 | 72 | 90 | 108 | 126 | 144 | 162 | 180 | 198
17.5 | 10.5 | 21 | 42 | 63 | 84 | 105 | 126 | 147 | 168 | 189 | 210 | 231
20 | 12 | 24 | 48 | 72 | 96 | 120 | 144 | 168 | 192 | 216 | 240 | 264

Dobutamine Injection USP Infusion Rate (mL/h) for 1000 mcg/mL concentration

Drug Delivery Rate |  |  |  | Patient Body Weight (kg)
(mcg/kg/min) | 5 | 10 | 20 | 30 | 40 | 50 | 60 | 70 | 80 | 90 | 100 | 110
0.5 | 0.1 | 0.3 | 0.6 | 0.9 | 1.2 | 1.5 | 1.8 | 2.1 | 2.4 | 2.7 | 3 | 3.3
1 | 0.3 | 0.6 | 1.2 | 1.8 | 2.4 | 3 | 3.6 | 4.2 | 4.8 | 5.4 | 6 | 6.6
2.5 | 0.7 | 1.5 | 3 | 4.5 | 6 | 7.5 | 9 | 10.5 | 12 | 13.5 | 15 | 16.5
5 | 1.5 | 3 | 6 | 9 | 12 | 15 | 18 | 21 | 24 | 27 | 30 | 33
7.5 | 2.2 | 4.5 | 9 | 13.5 | 18 | 22.5 | 27 | 31.5 | 36 | 40.5 | 45 | 49.5
10 | 3 | 6 | 12 | 18 | 24 | 30 | 36 | 42 | 48 | 54 | 60 | 66
12.5 | 3.7 | 7.5 | 15 | 22.5 | 30 | 37.5 | 45 | 52.5 | 60 | 67.5 | 75 | 82.5
15 | 4.5 | 9 | 18 | 27 | 36 | 45 | 54 | 63 | 72 | 81 | 90 | 99
17.5 | 5.2 | 10.5 | 21 | 31.5 | 42 | 52.5 | 63 | 73.5 | 84 | 94.5 | 105 | 115.5
20 | 6 | 12 | 24 | 36 | 48 | 60 | 72 | 84 | 96 | 108 | 120 | 132

Dobutamine Injection USP Infusion Rate (mL/h) for 2000 mcg/mL concentration

Drug Delivery Rate |  |  |  | Patient Body Weight (kg)
(mcg/kg/min) | 5 | 10 | 20 | 30 | 40 | 50 | 60 | 70 | 80 | 90 | 100 | 110
0.5 | 0.07 | 0.1 | 0.3 | 0.4 | 0.6 | 0.7 | 0.9 | 1 | 1.2 | 1.3 | 1.5 | 1.6
1 | 0.1 | 0.3 | 0.6 | 0.9 | 1.2 | 1.5 | 1.8 | 2.1 | 2.4 | 2.7 | 3 | 3.3
2.5 | 0.4 | 0.7 | 1.5 | 2 | 3 | 4 | 4.5 | 5 | 6 | 7 | 7.5 | 8
5 | 0.7 | 1.5 | 3 | 4.5 | 6 | 7.5 | 9 | 10.5 | 12 | 13.5 | 15 | 16.5
7.5 | 1.1 | 2.2 | 4.5 | 7 | 9 | 11 | 13.5 | 16 | 18 | 20 | 22.5 | 25
10 | 1.5 | 3 | 6 | 9 | 12 | 15 | 18 | 21 | 24 | 27 | 30 | 33
12.5 | 1.9 | 3.7 | 7 | 11 | 15 | 19 | 22.5 | 26 | 30 | 34 | 37.5 | 41
15 | 2.2 | 4.5 | 9 | 13.5 | 18 | 22.5 | 27 | 31.5 | 36 | 40.5 | 45 | 49.5
17.5 | 2.6 | 5.2 | 10.5 | 15.7 | 21 | 26.2 | 31.5 | 36.7 | 42 | 47.2 | 52.5 | 57.7
20 | 3 | 6 | 12 | 18 | 24 | 30 | 36 | 42 | 48 | 54 | 60 | 66

Concentrations of up to 5,000 mcg/mL have been administered to humans (250 mg/50 mL). The final volume administered should be determined by the fluid requirements of the patient.

Parenteral drug products should be inspected visually for particulate matter and discoloration prior to administration, whenever solution and container permit.

HOW SUPPLIED

Dobutamine Injection USP, 20 mL single dose vial contains dobutamine hydrochloride, equivalent to 250 mg dobutamine per 20 mL; ten vials per carton. NDC 0143-9141-10.

Store at 20° to 25°C (68° to 77°F) [see USP Controlled Room Temperature].

Manufactured by:

HIKMA FARMACÊUTICA (PORTUGAL), S.A.

Estrada do Rio da Mó, 8, 8A e 8B – Fervença – 2705-906 Terrugem SNT, PORTUGAL

Distributed by:

Hikma Pharmaceuticals USA Inc.

Berkeley Heights, NJ 07922

April 2024 PIN612-WES/2

PRINCIPAL DISPLAY PANEL

NDC 0143-9141-01 Rx only

DOBUTamine
Injection, USP
250 mg per 20 mL (12.5 mg/mL)
For Intravenous Use ONLY
Must be diluted prior to use
Use within 24 hours after dilution
20 mL Single-Dose Vial

NDC 0143-9141-10 Rx only

DOBUTamine
Injection, USP
250 mg per 20 mL (12.5 mg/mL)
For Intravenous Use ONLY
Must be diluted prior to use
Use within 24 hours after dilution
10 x 20 mL Single-Dose Vials